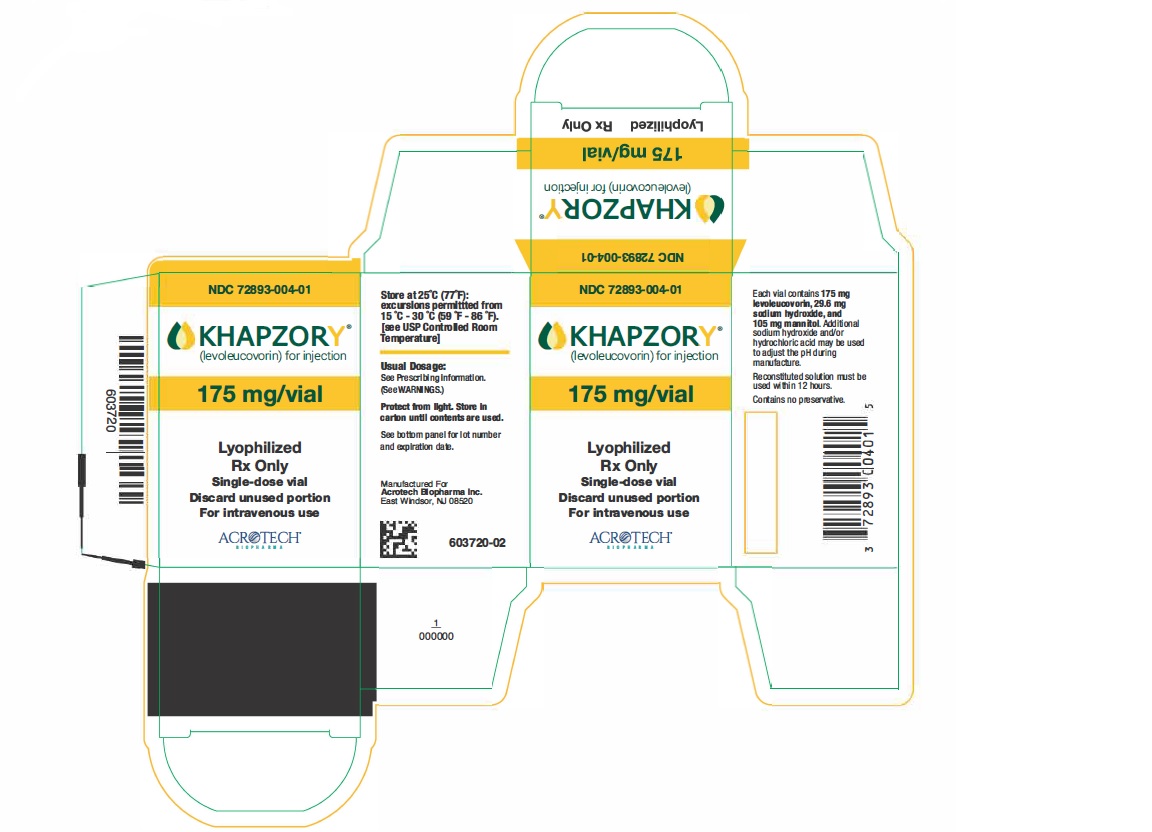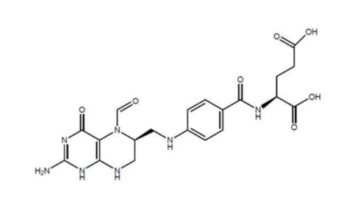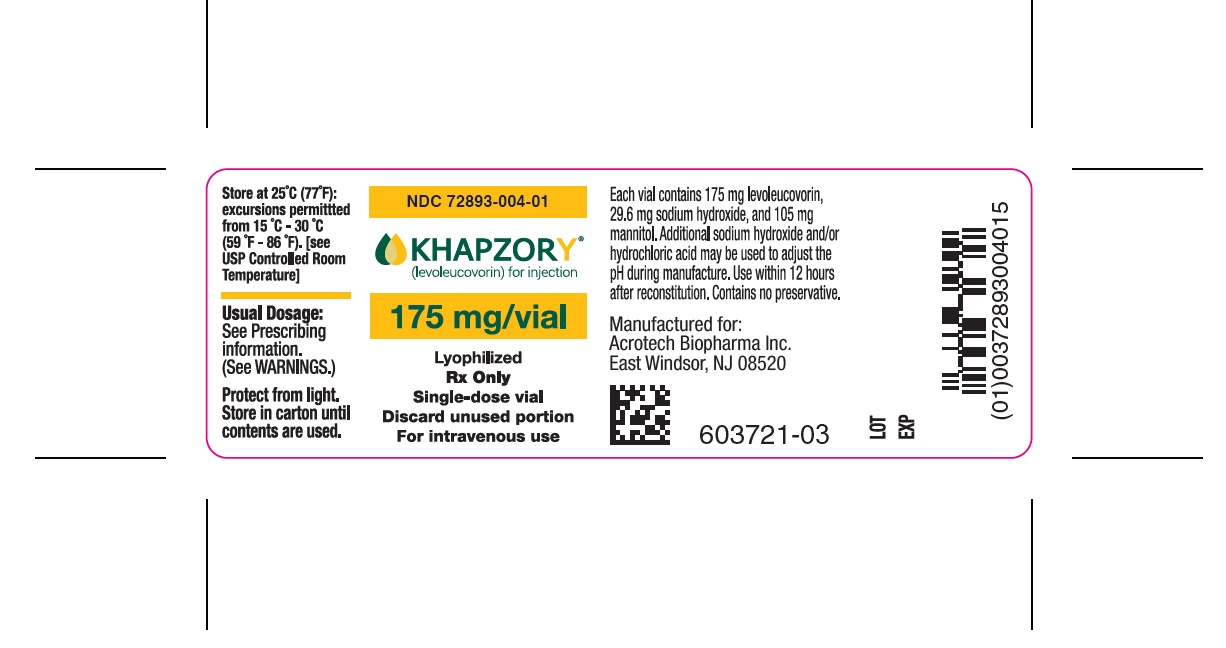 DRUG LABEL: KHAPZORY
NDC: 72893-004 | Form: INJECTION, POWDER, LYOPHILIZED, FOR SOLUTION
Manufacturer: Acrotech Biopharma Inc
Category: prescription | Type: Human Prescription Drug Label
Date: 20241212

ACTIVE INGREDIENTS: LEVOLEUCOVORIN DISODIUM 175 mg/3.5 mL
INACTIVE INGREDIENTS: SODIUM HYDROXIDE 29.6 mg/3.5 mL; MANNITOL 105 mg/3.5 mL

HIGHLIGHTS OF PRESCRIBING INFORMATION

These highlights do not include all the information needed to use KHAPZORY® safely and effectively. See full prescribing information for KHAPZORY.
KHAPZORY (levoleucovorin) for injection, for intravenous use
Initial U.S. Approval: 1952 (d,l-leucovorin)

1 INDICATIONS AND USAGE

KHAPZORY is a folate analog indicated for:

- Rescue after high-dose methotrexate therapy in adults and pediatric patients with osteosarcoma. (1)
- Diminishing the toxicity associated with overdosage of folic acid antagonists or impaired methotrexate elimination in adult and pediatric patients. (1)
- Treatment of adults with metastatic colorectal cancer in combination with fluorouracil. (1)

Limitations of Use

KHAPZORY is not indicated for pernicious anemia and megaloblastic anemia secondary to lack of vitamin B12 because of the risk of progression of neurologic manifestations despite hematologic remission.(1)

2 DOSAGE AND ADMINISTRATION

For intravenous administration only. Do not administer intrathecally. (2.1)

Rescue After High-Dose Methotrexate Therapy

- Rescue recommendations are based on a methotrexate dose of 12 grams/ m^2 administered by intravenous infusion over 4 hours. Initiate rescue at a dose of 7.5 mg (approximately 5 mg/m^2) every 6 hours, 24 hours after the beginning of the methotrexate infusion. (2.2)
- Continue until the methotrexate level is below 5 x 10^-8 M (0.05 micromolar). Adjust dose if necessary, based on methotrexate elimination; refer to Full Prescribing Information. (2.2)

Overdosage of Folic Acid Antagonists or Impaired Methotrexate Elimination

- Start as soon as possible after methotrexate overdosage or within 24 hours of delayed methotrexate elimination. (2.3)
- Administer KHAPZORY 7.5 mg (approximately 5 mg/m^2) intravenously every 6 hours until methotrexate level is less than 5 x 10^-8 M (0.05 micromolar). (2.3)

Metastatic Colorectal Cancer in Combination with Fluorouracil

- The following regimens have been used for the treatment of colorectal cancer.
  - KHAPZORY 100 mg/m^2 by intravenous injection over a minimum of 3 minutes, followed by fluorouracil 370 mg/m^2 once daily for 5 consecutive days. (2.4)
  - KHAPZORY 10 mg/m^2 by intravenous injection followed by fluorouracil 425 mg/m^2 once daily for 5 consecutive days. (2.4)

- The above five-day courses may be repeated every 4 weeks for 2 courses, then every 4 to 5 weeks, if the patient has recovered from toxicity from the prior course. (2.4)
- Do not adjust KHAPZORY dosage for toxicity. (2.4)

3 DOSAGE FORMS AND STRENGTHS

For Injection: 175 mg of levoleucovorin lyophilized powder in a single-dose vial for reconstitution. (3)

4 CONTRAINDICATIONS

Patients who have had severe hypersensitivity reactions to leucovorin products, folic acid, or folinic acid. (4)

5 WARNINGS AND PRECAUTIONS

- Increased Gastrointestinal Toxicities with Fluorouracil: Do not initiate or continue therapy with KHAPZORY and fluorouracil in patients with symptoms of gastrointestinal toxicity until symptoms have resolved. Monitor patients with diarrhea until it has resolved as rapid deterioration leading to death can occur. (5.1,7)
- Drug Interaction with Trimethoprim-Sulfamethoxazole: Increased rates of treatment failure and morbidity with concomitant use of d,l-leucovorin with trimethoprim-sulfamethoxazole for Pneumocystis jiroveci pneumonia in patients with HIV. (5.2)

6 ADVERSE REACTIONS

- The most common adverse reactions (≥ 20%) in patients receiving high-dose methotrexate therapy with levoleucovorin rescue are stomatitis and vomiting. (6.1)
- The most common adverse reactions (>50%) in patients receiving levoleucovorin in combination with fluorouracil for metastatic colorectal cancer are stomatitis, diarrhea, and nausea. (6.1)

To report SUSPECTED ADVERSE REACTIONS, contact Acrotech Biopharma Inc at 1-888-292-9617 or FDA at 1-800-FDA-1088 or www.fda.gov/medwatch.

FULL PRESCRIBING INFORMATION

1 INDICATIONS AND USAGE

KHAPZORY is indicated for:

- rescue after high-dose methotrexate therapy in adult and pediatric patients with osteosarcoma.
- diminishing the toxicity associated with overdosage of folic acid antagonists or impaired methotrexate elimination adult and pediatric patients.
- The treatment of adults with metastatic colorectal cancer in combination with fluorouracil.

Limitations of Use

KHAPZORY is not indicated for pernicious anemia and megaloblastic anemia secondary to lack the of vitamin B12 because of the risk of progression of neurologic manifestations despite hematologic remission.

2 DOSAGE AND ADMINISTRATION

2.1 Important Use Information

KHAPZORY is indicated for intravenous administration only. Do not administer intrathecally.

2.2 Recommended Dosage for Rescue After High-Dose Methotrexate Therapy

The recommended dosage for KHAPZORY is based on a methotrexate dose of 12 grams/m^2 administered as intravenous infusion over 4 hours. Twenty-four hours after starting the methotrexate infusion, initiate KHAPZORY at a dose of 7.5 mg (approximately 5 mg/m^2) as an intravenous infusion every 6 hours.

Monitor serum creatinine and methotrexate levels at least once daily. Continue KHAPZORY, hydration, and urinary alkalinization (pH of 7 or greater) until the methotrexate level is below 5 x 10^-8 M (0.05 micromolar). Adjust the dose KHAPZORY or extend the duration as recommended in Table 1.

Table 1 Recommended Dosage for KHAPZORY based on Serum Methotrexate and Creatinine Levels
Clinical Situation | Laboratory Findings | Recommendation
Normal methotrexate elimination | Serum methotrexate level approximately 10 micromolar at 24 hours after administration, 1 micromolar at 48 hours, and less than 0.2 micromolar at 72 hours. | Administer 7.5 mg by intravenous infusion every 6 hours for 60 hours (10 doses starting at 24 hours after start of methotrexate infusion).
Delayed late methotrexate elimination | Serum methotrexate level remaining above 0.2 micromolar at 72 hours, and more than 0.05 micromolar at 96 hours after administration. | Continue 7.5 mg by intravenous infusion every 6 hours, until methotrexate level is less than 0.05 micromolar.
Delayed early methotrexate elimination and/or evidence of acute renal injury* | Serum methotrexate level of 50 micromolar or more at 24 hours, or 5 micromolar or more at 48 hours after administration, OR 100% or greater increase in serum creatinine level at 24 hours after methotrexate administration (e.g., an increase from 0.5 mg/dL to a level of 1 mg/dL or more). | Administer 75 mg by intravenous infusion every 3 hours until methotrexate level is less than 1 micromolar; then 7.5 mg by intravenous infusion every 3 hours until methotrexate level is less than 0.05 micromolar.

*These patients are likely to develop reversible renal failure. In addition to appropriate KHAPZORY therapy, continue hydration and urinary alkalinization, and monitoring fluid and electrolyte status, until the serum methotrexate level has fallen to below 0.05 micromolar and the renal failure has resolved.

Impaired Methotrexate Elimination or Renal Impairment

Decreased methotrexate elimination or renal impairment which are clinically important but less severe than the abnormalities described in Table 1 can occur following methotrexate administration. If toxicity associated with methotrexate is observed, in subsequent courses extend KHAPZORY rescue for an additional 24 hours (total of 14 doses over 84 hours).

Third-Space Fluid Collection and Other Causes of Delayed Methotrexate Elimination

Accumulation in a third space fluid collection (i.e., ascites, pleural effusion), renal insufficiency, or inadequate hydration can delay methotrexate elimination. Under such circumstances, higher doses of KHAPZORY or prolonged administration may be indicated.

2.3 Recommended Dosage for Overdosage of Folic Acid Antagonists or Impaired Methotrexate Elimination

Start KHAPZORY as soon as possible after an overdosage of methotrexate or within 24 hours of methotrexate administration when methotrexate elimination is impaired. As the time interval between methotrexate administration and KHAPZORY increases, the effectiveness of KHAPZORY to diminish methotrexate toxicity may decrease. Administer KHAPZORY 7.5 mg (approximately 5 mg/m^2) as an intravenous infusion every 6 hours until the serum methotrexate level is less than 5 x 10^-8 M (0.05 micromolar).

Monitor serum creatinine and methotrexate levels at least every 24 hours. Increase the dosage of KHAPZORY to 50 mg/m^2 intravenously every 3 hours and continue KHAPZORY at this dosage until the methotrexate level is less than 5 x 10^-8 M for the following:

- if the serum creatinine at 24-hours increases 50% or more compared to baseline
- if the methotrexate level at 24-hours is greater than 5 x 10^-6 M
- if the methotrexate level at 48-hours is greater than 9 x 10^-7 M

Continue concomitant hydration (3 L per day) and urinary alkalinization with sodium bicarbonate. Adjust the bicarbonate dose to maintain urine pH at 7 or greater.

2.4 Dosage in Combination with Fluorouracil for Metastatic Colorectal Cancer

The following regimens have been used for the treatment of colorectal cancer:

- KHAPZORY 100 mg/m^2 by intravenous injection over a minimum of 3 minutes, followed by fluorouracil at 370 mg/m^2 by intravenous injection , once daily for 5 consecutive days
- KHAPZORY at 10 mg/m^2 by intravenous injection, followed by fluorouracil at 425 mg/m^2,by intravenous injection once daily for 5 consecutive days

This five-day course may be repeated every 4 weeks for 2 courses, then every 4 to 5 weeks, if the patient has recovered from toxicity from the prior course. Do not adjust KHAPZORY dosage for toxicity.

Refer to fluorouracil prescribing information for information on fluorouracil dosage and dosage modifications for adverse reactions.

2.5 Preparation

Reconstitute the 175 mg vial contents with 3.6 mL of 0.9% Sodium Chloride Injection, USP, to obtain a clear, colorless to yellowish solution (resultant concentration 50 mg per mL levoleucovorin). Reconstitution with a sodium chloride solution with preservatives (e.g., benzyl alcohol) has not been studied. Do not store reconstituted solution for more than 12 hours at room temperature. Protect from light.

Dilute reconstituted solution immediately (if possible), to concentrations of 0.5 mg/mL to 5 mg/mL in 0.9% Sodium Chloride Injection, USP or 5% Dextrose Injection, USP. Do not store the diluted reconstituted solution for more than 12 hours at room temperature. Protect from light.

Visually inspect the product for particulate matter and discoloration prior to administration. Discard if particulate matter or discoloration is observed.

3 DOSAGE FORMS AND STRENGTHS

For Injection: 175 mg of levoleucovorin as a sterile, white to yellowish lyophilized powder in a single-dose vial for reconstitution.

4 CONTRAINDICATIONS

KHAPZORY is contraindicated in patients who have had severe hypersensitivity to leucovorin products, folic acid, or folinic acid [see Adverse Reactions (6.2)].

5 WARNINGS AND PRECAUTIONS

5.1 Increased Gastrointestinal Toxicities with Fluorouracil

Leucovorin products increase the toxicities of fluorouracil [see Drug Interactions (7)]. Gastrointestinal toxicities, including stomatitis and diarrhea, occur more commonly and may be of greater severity and of prolonged duration. Deaths from severe enterocolitis, diarrhea, and dehydration have occurred in elderly patients receiving weekly d,l-leucovorin and fluorouracil.

Monitor patients for gastrointestinal toxicities. Do not initiate or continue therapy with KHAPZORY and fluorouracil in patients with symptoms of gastrointestinal toxicity until those symptoms have resolved. Monitor patients with diarrhea until it has resolved as rapid deterioration leading to death can occur.

5.2 Drug Interaction with Trimethoprim-Sulfamethoxazole

The concomitant use of d,l-leucovorin with trimethoprim-sulfamethoxazole for the acute treatment of Pneumocystis jiroveci pneumonia in patients with HIV infection was associated with increased rates of treatment failure and morbidity [ see Drug Interation (7)].

6 ADVERSE REACTIONS

The following clinical significant adverse reactions are described elsewhere in the labeling:

- Increased gastrointestinal toxicities with fluorouracil [see Warnings and Precautions (5.1)]

6.1 Clinical Trials Experience

Because clinical trials are conducted under widely varying conditions, adverse reaction rates observed in the clinical trials of a drug cannot be directly compared to rates in the clinical trials of another drug and may not reflect the rates observed in practice.

High-Dose Methotrexate Therapy

Table 2 presents the frequency of adverse reactions which occurred during the administration of 58 courses of high-dose methotrexate 12 grams/m^2 followed by levoleucovorin rescue, for osteosarcoma, in 16 patients aged 6 to 21 years. Most patients received levoleucovorin 7.5 mg every 6 hours for 60 hours or longer, beginning 24 hours after completion of methotrexate administration.

Table 2 Adverse Reactions with High-Dose Methotrexate Therapy
Adverse Reactions | Levoleucovorin n=16
Adverse Reactions | All Grades (%) | Grade 3-4 (%)
Gastrointestinal
Stomatitis | 38 | 6
Vomiting | 38 | 0
Nausea | 19 | 0
Diarrhea | 6 | 0
Dyspepsia | 6 | 0
Typhlitis | 6 | 6
Respiratory
Dyspnea | 6 | 0
Skin and Appendages
Dermatitis | 6 | 0
Other
Confusion | 6 | 0
Neuropathy | 6 | 0
Renal function abnormal | 6 | 0
Taste perversion | 6 | 0

Combination with Fluorouracil in Colorectal Cancer

Table 3 presents the frequency of adverse reactions which occurred in 2 arms of a randomized controlled trial conducted by the North Central Cancer Treatment Group (NCCTG) in patients with metastatic colorectal cancer. The trial failed to show superior overall survival with fluorouracil + levoleucovorin compared to fluorouracil + d,l-leucovorin. Patients were randomized to fluorouracil 370 mg/m^2 intravenously and levoleucovorin 100 mg/m^2 intravenously, both daily for 5 days, or to fluorouracil 370 mg/m^2 intravenously and d,l-leucovorin 200 mg/m^2 intravenously, both daily for 5 days. Treatment was repeated week 4 and week 8, and then every 5 weeks until disease progression or unacceptable toxicity.

Table 3 Adverse Reactions Occurring in ≥ 10% of Patients in Either Arm
Adverse Reactions | Levoleucovorin/ fluorouracil n=318 |  | d,l-Leucovorin/ fluorouracil n=307
Adverse Reactions | Grades 1-4 (%) | Grades 3-4 (%) | Grades 1-4 (%) | Grades 3-4 (%)
Gastrointestinal Disorders
Stomatitis | 72 | 12 | 72 | 14
Diarrhea | 70 | 19 | 65 | 17
Nausea | 62 | 8 | 61 | 8
Vomiting | 40 | 5 | 37 | 6
Abdominal Pain* | 14 | 3 | 19 | 3
General Disorders
Asthenia/Fatigue/Malaise | 29 | 5 | 32 | 11
Skin Disorders
Dermatitis | 29 | 1 | 28 | 1
Alopecia | 26 | 0.3 | 28 | 1
Metabolism and Nutrition
Anorexia/Decreased Appetite | 24 | 4 | 25 | 2

*Includes abdominal pain, upper abdominal pain, lower abdominal pain, and abdominal tenderness

6.2 Postmarketing Experience

The following adverse reactions have been identified during post-approval use of levoleucovorin products. Because these adverse reactions are reported voluntarily from a population of uncertain size, it is not always possible to reliably estimate their frequency or establish a causal relationship to drug exposure. The following have been reported:

- Dermatologic: pruritus, rash
- Respiratory: dyspnea
- Other Clinical Events: temperature change, rigors, allergic reactions

7 DRUG INTERACTIONS

7.1 Effects of Leucovorin Products on Other Drugs

Antiepileptic Drugs
Folic acid in large amounts may counteract the antiepileptic effect of phenobarbital, phenytoin and primidone and increase the frequency of seizures in susceptible children. It is not known whether folinic acid has the same effects; however, both folic and folinic acids share some common metabolic pathways. Monitor patients taking folinic acid in combination with antiepileptic drugs.

Fluorouracil
Leucovorin products increase the toxicity of fluorouracil. Do not initiate or continue therapy with Fusilev and fluorouracil in patients with symptoms of gastrointestinal toxicity until those symptoms have resolved. Monitor patients with diarrhea until the diarrhea has resolved, as rapid deterioration leading to death can occur [see Warnings and Precautions (5.2)].

Trimethoprim-Sulfamethoxazole
The concomitant use of d,l-leucovorin with trimethoprim-sulfamethoxazole for the acute treatment of Pneumocystis jiroveci pneumonia in patients with HIV infection was associated with increased rates of treatment failure and morbidity in a placebo-controlled study [see Warnings and Precautions (5)].

8 USE IN SPECIFIC POPULATIONS

8.1 Pregnancy

Risk Summary

There are limited data with levoleucovorin use in pregnant women. Animal reproduction studies have not been conducted with levoleucovorin.

Levoleucovorin is administered in combination with methotrexate or fluorouracil, which can cause embryo-fetal harm. Refer to methotrexate or fluorouracil prescribing information for additional information.

In the U.S. general population, the estimated background risk of major birth defects and miscarriage in clinically recognized pregnancies is 2% to 4% and 15% to 20%, respectively.

8.2 Lactation

Risk Summary

There are no data on the presence of levoleucovorin in human milk or its effects on the breastfed infant or on milk production.

Levoleucovorin is administered in combination with methotrexate or fluorouracil. Refer to methotrexate or fluorouracil prescribing information for additional information.

8.4 Pediatric Use

The safety and effectiveness of KHAPZORY have been established in pediatric patients for rescue after high-dose methotrexate therapy in osteosarcoma and diminishing the toxicity associated with overdosage of folic acid antagonists or impaired methotrexate elimination. Use of levoleucovorin in pediatric patients is supported by open-label clinical trial data in 16 pediatric patients 6 years of age and older, with additional supporting evidence from literature [see Clinical Studies (14.1)].

The safety and effectiveness of KHAPZORY have not been established for the treatment of pediatric patients with advanced metastatic colorectal cancer.

8.5 Geriatric Use

Clinical studies of levoleucovorin in the treatment of osteosarcoma did not include patients aged 65 years and over to determine whether they respond differently from younger patients.

In the NCCTG clinical trial of levoleucovorin in combination with fluorouracil in the treatment of metastatic colorectal cancer, adverse reactions were consistent with fluorouracil related toxicity and were similar for patients age 65 years and older and patients younger than 65 [see Clinical Studies (14.2)].

11 DESCRIPTION

Levoleucovorin is a folate analog and the pharmacologically active levo-isomer of d,l-leucovorin. The chemical name is (2S)-2-[[4-[[(6S)-2-amino-5-formyl-4-oxo-1,6,7,8-tetrahydropteridin-6- yl] methylamino] benzoyl] amino] pentanedioate. The molecular formula is C20H23N7O7 and the molecular weight is 473.45. The molecular structure is:

Levoleucovorin is a slightly hygroscopic, crystalline, yellow powder which is soluble in water when pH is at or above 8.

KHAPZORY 175 mg is a sterile lyophilized powder consisting of 175 mg levoleucovorin, 29.6 mg sodium hydroxide, and 105 mg mannitol in each vial. Additional sodium hydroxide and/or hydrochloric acid may be used to adjust the pH during manufacture. It is intended for intravenous administration after reconstitution with 3.6 mL of sterile 0.9% Sodium Chloride Injection, USP.

12 CLINICAL PHARMACOLOGY

12.1 Mechanism of Action

High-Dose Methotrexate Therapy

Levoleucovorin is the pharmacologically active isomer of 5-formyl tetrahydrofolic acid. Levoleucovorin does not require reduction by dihydrofolate reductase to participate in reactions utilizing folates as a source of “one-carbon” moieties. Administration of levoleucovorin counteracts the therapeutic and toxic effects of folic acid antagonists such as methotrexate, which act by inhibiting dihydrofolate reductase.

Combination with Fluorouracil in Colorectal Cancer

Levoleucovorin enhances the therapeutic and toxic effects of fluorouracil. Fluorouracil is metabolized to 5-fluoro-2'-deoxyuridine-5'-monophosphate (FdUMP), which binds to and inhibits thymidylate synthase (an enzyme important in DNA repair and replication). Levoleucovorin is converted to another reduced folate, 5,10-methylenetetrahydrofolate, which then acts to stabilize the binding of FdUMP to thymidylate synthase, thereby enhancing the inhibition of thymidylate synthase.

12.3 Pharmacokinetics

The pharmacokinetics of levoleucovorin after intravenous injection of a 15 mg dose was studied in healthy subjects. The mean maximum serum total tetrahydrofolate (total-THF) concentration was 1722 ng/mL (CV 39%) and the mean maximum serum (6S)-5-methyl-5,6,7,8-tetrahydrofolate concentration was 275 ng/mL (CV 18%) observed around 0.9 hours post injection.

Distribution
Exploratory studies show that small quantities of systemically administered leucovorin enter the cerebrospinal fluid (CSF), primarily as its major metabolite 5-methyltetrahydrofolate (5-MTHFA). In humans, the CSF levels of 5-MTHFA remain 1-3 orders of magnitude lower than the usual methotrexate concentrations following intrathecal administration.

Elimination
The mean terminal half-life was 5.1 hours for total-THF and 6.8 hours for (6S)-5-methyl-5,6,7,8-tetrahydrofolate.

Drug Interaction Studies
The mean dose-normalized steady-state plasma concentrations for both levoleucovorin and 5-methyl-THF were comparable whether fluorouracil (370 mg/m^2/day as an intravenous bolus) was given in combination with levoleucovorin (250 mg/m^2 and 1000 mg/m^2 as a continuous intravenous infusion for 5.5 days) or in combination with d,l-leucovorin (500 mg/m^2 as a continuous intravenous infusion for 5.5 days).

13 NONCLINICAL TOXICOLOGY

13.1 Carcinogenesis, Mutagenesis, Impairment of Fertility

No studies have been conducted to evaluate the potential of levoleucovorin for carcinogenesis, mutagenesis and impairment of fertility.

14 CLINICAL STUDIES

14.1 Rescue after High-Dose Methotrexate Therapy in Patients with Osteosarcoma

The efficacy of levoleucovorin rescue following high-dose methotrexate were evaluated in 16 patients aged 6 to 21 years, who received 58 courses of therapy for osteogenic sarcoma. High-dose methotrexate was one component of several different combination chemotherapy regimens evaluated across several trials. Methotrexate 12 g/m^2 as an intravenous infusion over 4 hours was administered to 13 patients, who received levoleucovorin 7.5 mg every 6 hours for 60 hours or longer beginning 24 hours after completion of methotrexate. Three patients received methotrexate 12.5 g/m^2 intravenously over 6 hours, followed by levoleucovorin 7.5 mg by intravenous infusion every 3 hours for 18 doses beginning 12 hours after completion of methotrexate. The mean number of levoleucovorin doses per course was 18.2 and the mean total dose per course was 350 mg. The efficacy of levoleucovorin rescue following high-dose methotrexate was based on adverse reaction profile [see Adverse Reactions (6.1)].

14.2 Metastatic Colorectal Cancer

In a randomized clinical study conducted by the Mayo Clinic and the North Central Cancer Treatment Group (NCCTG) in patients with metastatic colorectal cancer comparing d,l leucovorin 200 mg/m^2 and fluorouracil 370 mg/m^2 versus leucovorin 20 mg/m^2 and fluorouracil 425 mg/m^2 versus fluorouracil 500 mg/m^2, with all drugs administered by intravenous infusion daily for 5 days every 28 to 35 days, response rates were 26% (p=0.04 versus fluorouracil alone), 43% (p=0.001 versus fluorouracil alone), and 10%, respectively. Respective median survival times were 12.2 months (p=0.037), 12 months (p=0.050), and 7.7 months. The low dose d,l-leucovorin regimen was associated with a statistically significant improvement in weight gain of more than 5%, relief of symptoms, and improvement in performance status. The high dose d,l-leucovorin regimen was associated with a statistically significant improvement in performance status and trended toward improvement in weight gain and in relief of symptoms but these were not statistically significant.

In a second randomized clinical study conducted by Mayo and NCCTG, the fluorouracil alone arm was replaced by sequentially administered methotrexate, fluorouracil, and d,l leucovorin . Response rates with d,l leucovorin 200 mg/m^2 and fluorouracil 370 mg/m^2 versus d,l leucovorin 20 mg/m^2 and fluorouracil 425 mg/m^2 versus sequential methotrexate and fluorouracil and d,l leucovorin were 31% (p≤0.01), 42% (p≤0.01), and 14%, respectively. Respective median survival times were 12.7 months (p≤0.04), 12.7 months (p≤0.01), and 8.4 months. There was no statistically significant difference in weight gain of more than 5% or in improvement in performance status between the treatment arms.

A randomized controlled study conducted by the NCCTG in patients with metastatic colorectal cancer failed to show superiority of a regimen of fluorouracil + levoleucovorin to fluorouracil + d,l-leucovorin in overall survival. Patients were randomized to fluorouracil 370 mg/m^2 intravenously and levoleucovorin 100 mg/m^2 intravenously, both daily for 5 days, or to fluorouracil 370 mg/m^2 intravenously and d,l-leucovorin 200 mg/m^2 intravenously, both daily for 5 days. Treatment was repeated week 4 and week 8, then every 5 weeks until disease progression or unacceptable toxicity.

16 HOW SUPPLIED/STORAGE AND HANDLING

KHAPZORY (levoleucovorin) for injection is a sterile, preservative-free, white to yellowish lyophilized powder in a single-dose vial. It is available as:

175 mg vial –NDC 72893-004-01.
Store at 20°C to 25°C (68°F to 77°F) in original carton until contents are used. Excursions permitted between 15°C and 30°C (59°F and 86°F) [see USP Controlled Room Temperature]. Protect solutions from light.

Distributed by:
Acrotech Biopharma Inc
East Windsor, NJ 08520

KHAPZORY is a registered trademark of Acrotech Biopharma Inc.

PACKAGE/LABEL PRINCIPAL DISPLAY PANEL

Carton Label

NDC 72893-004-01
KHAPZORY

175 mg/vial

For Intravenous use only

Single-dose vial

Vial Label

NDC 72893-004-01
KHAPZORY

175 mg/vial

For Intravenous use only

Single-dose vial